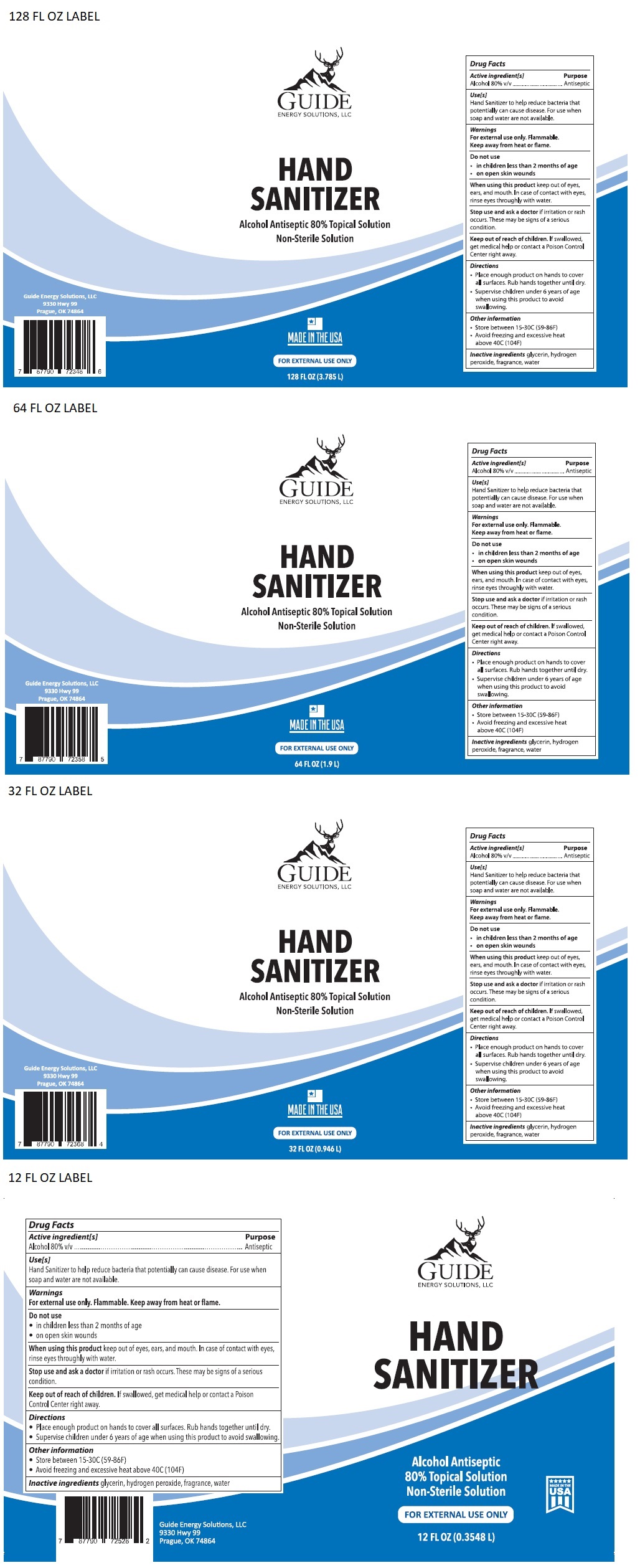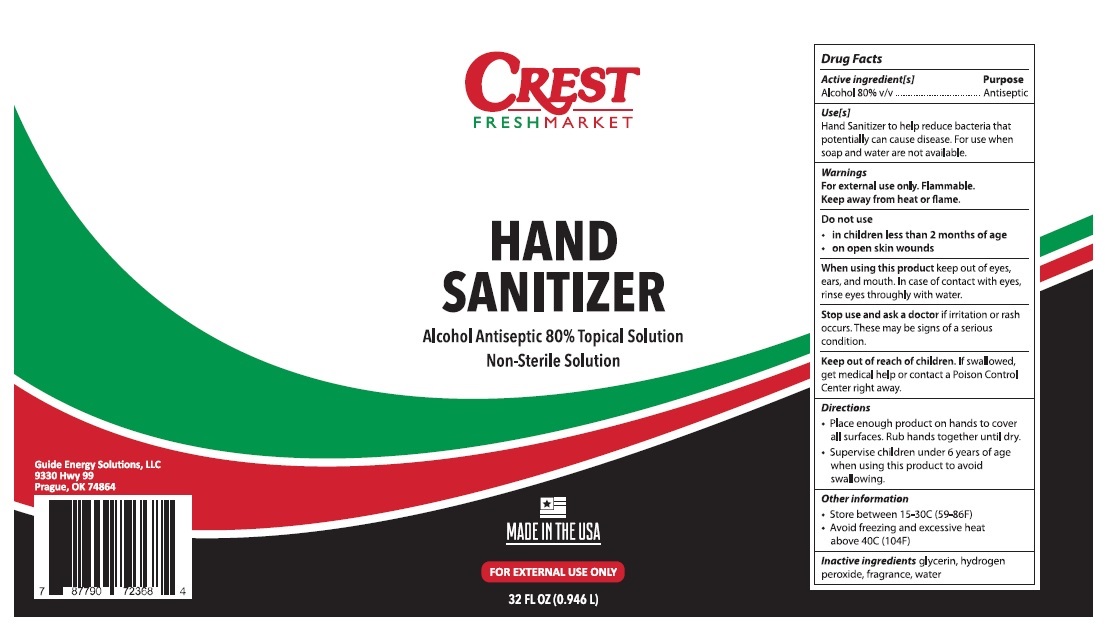 DRUG LABEL: Hand Sanitizer
NDC: 77042-180 | Form: SOLUTION
Manufacturer: Guide Energy Solutions LLC
Category: otc | Type: HUMAN OTC DRUG LABEL
Date: 20211228

ACTIVE INGREDIENTS: ALCOHOL 80 L/100 L
INACTIVE INGREDIENTS: GLYCERIN; HYDROGEN PEROXIDE; WATER

HAND SANITIZER

Active ingredient[s]

Alcohol 80% v/v

Purpose

Antiseptic

Use[s]

Hand Sanitizer to help reduce bacteria that potentially can cause disease. For use when soap and water are not available.

Warnings

For external use only. Flammable.

Keep away from heat or flame.

Do not use

• in children less than 2 months of age

• on open skin wounds

When using this product keep out of eyes, ears, and mouth. In case of contact with eyes, rinse eyes thoroughly with water.

Stop use and ask a doctor if irritation or rash occurs. These may be signs of a serious condition.

Keep out of reach of children. If swallowed, get medical help or contact a Poison Control Center right away.

Directions

• Place enough product on hands to cover all surfaces. Rub hands together until dry.

• Supervise children under 6 years of age when using this product to avoid swallowing.

Other information

• Store between 15-30°C (59-83°F)

• Avoid freezing and excessive heat above 40°C (104°F)

Inactive ingredients glycerin, hydrogen peroxide, fragrance, water

Alcohol Antiseptic 80% Topical Solution

Non-Sterile Solution

MADE IN THE USA

Guide Energy Solutions, LLC

9330 Hwy 99

Prague, OK 74864